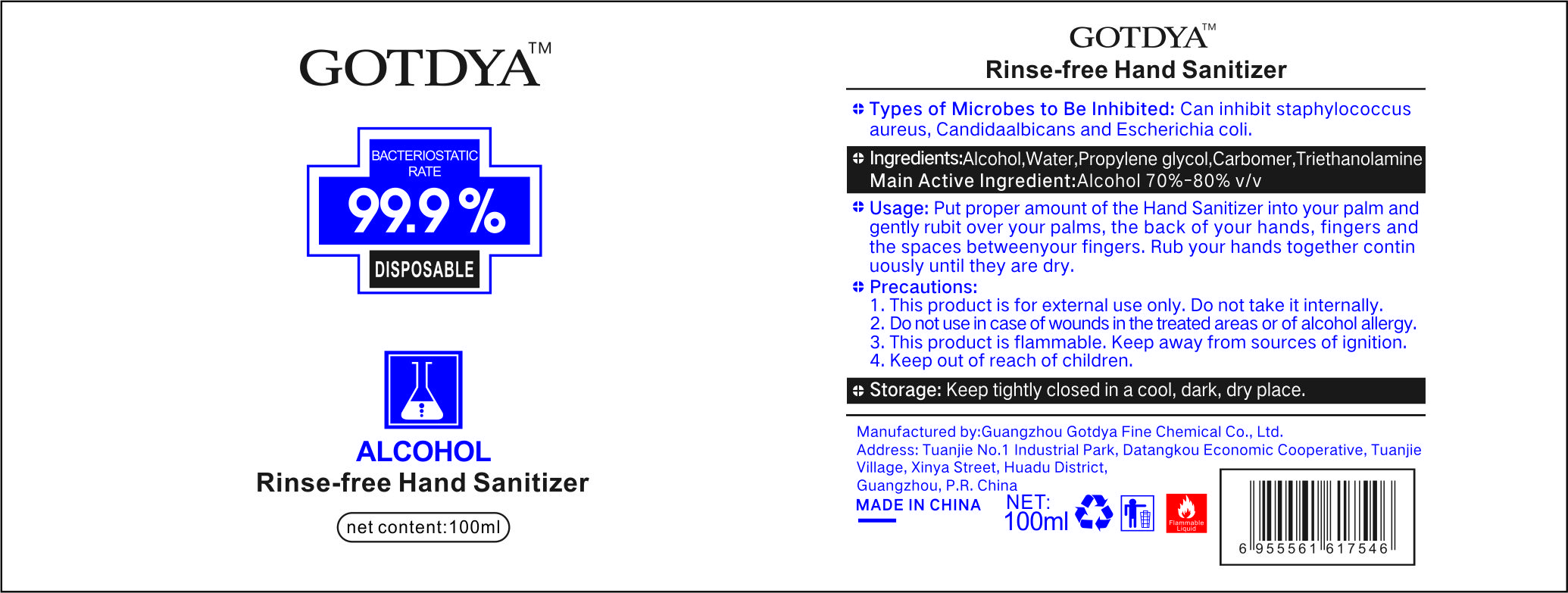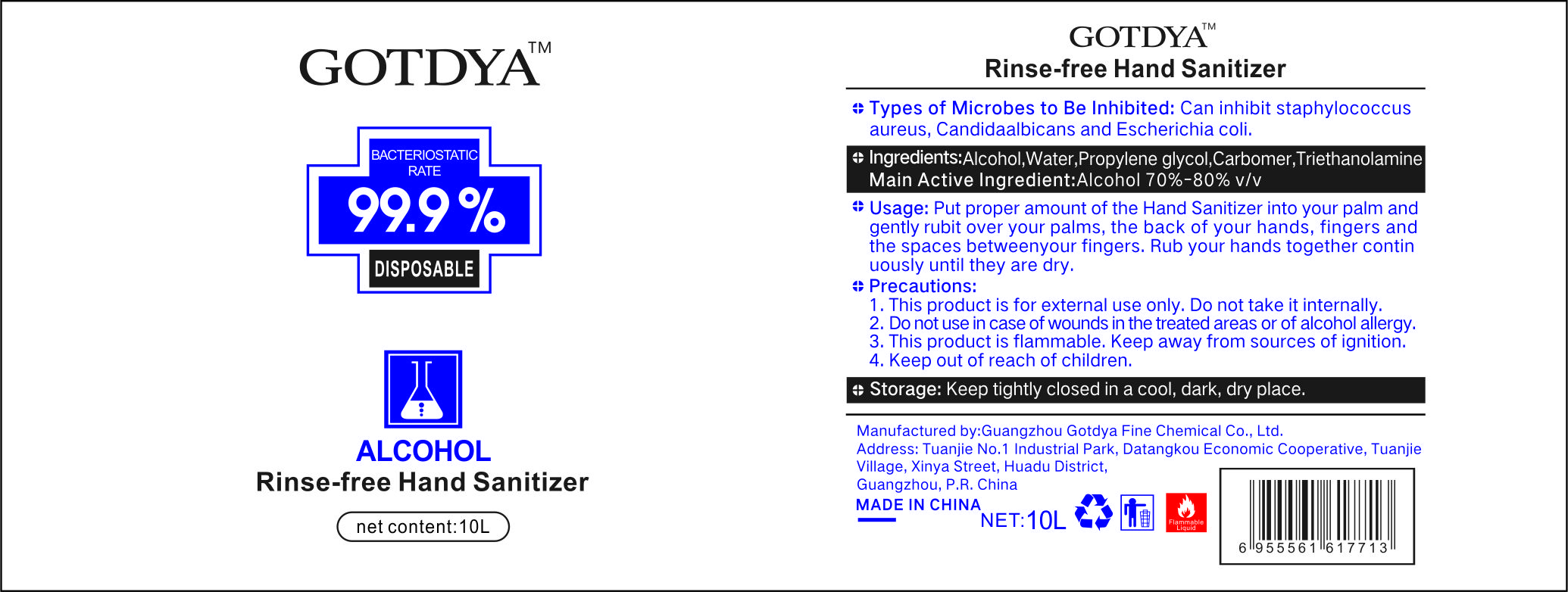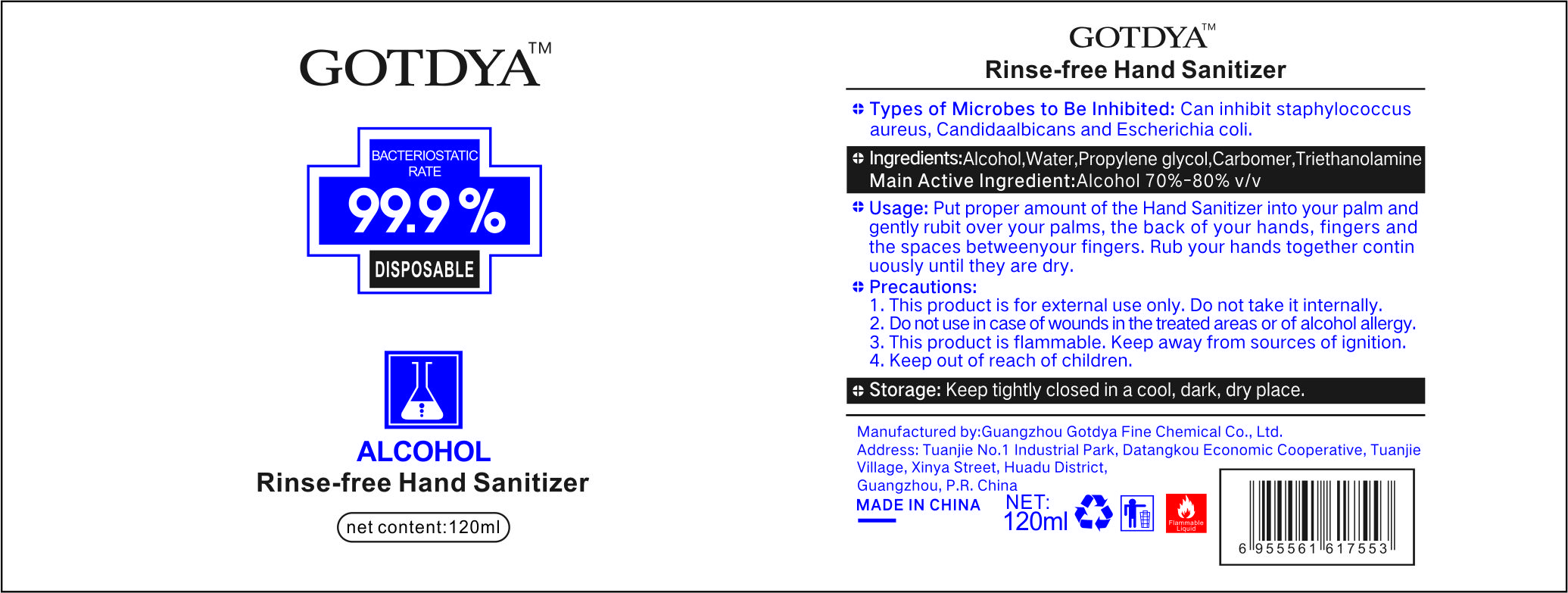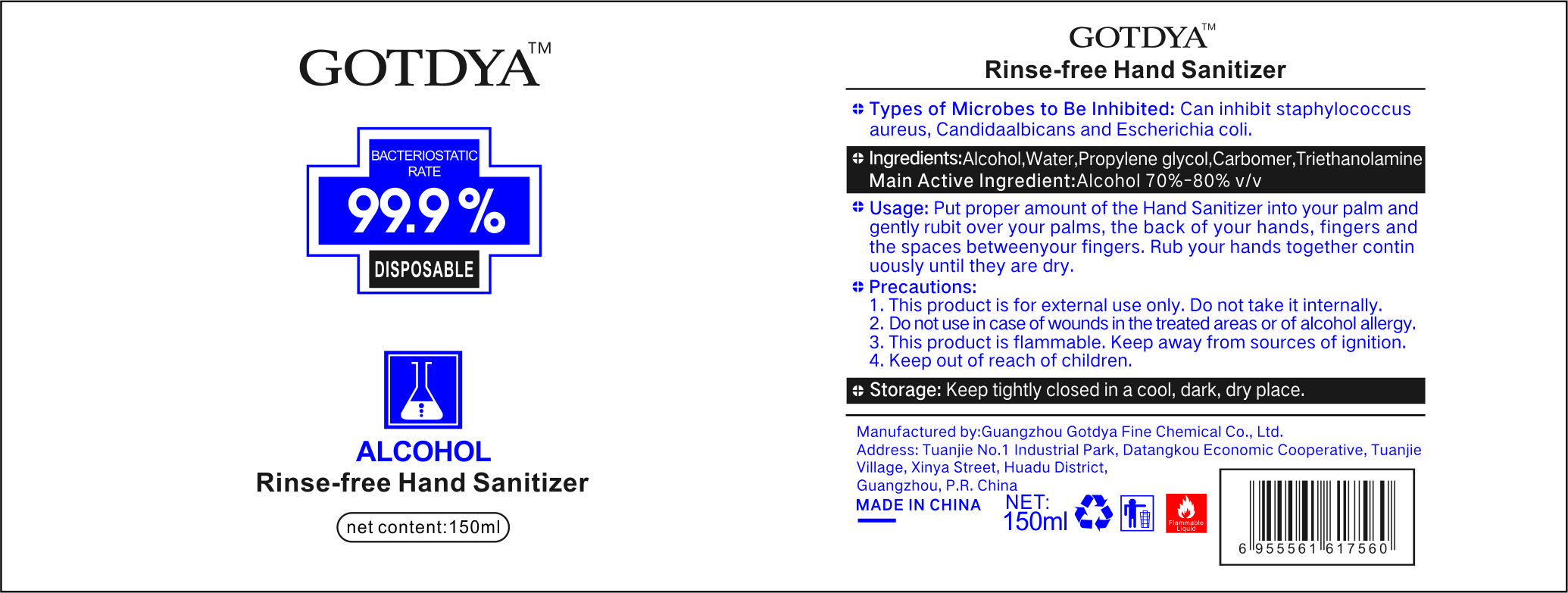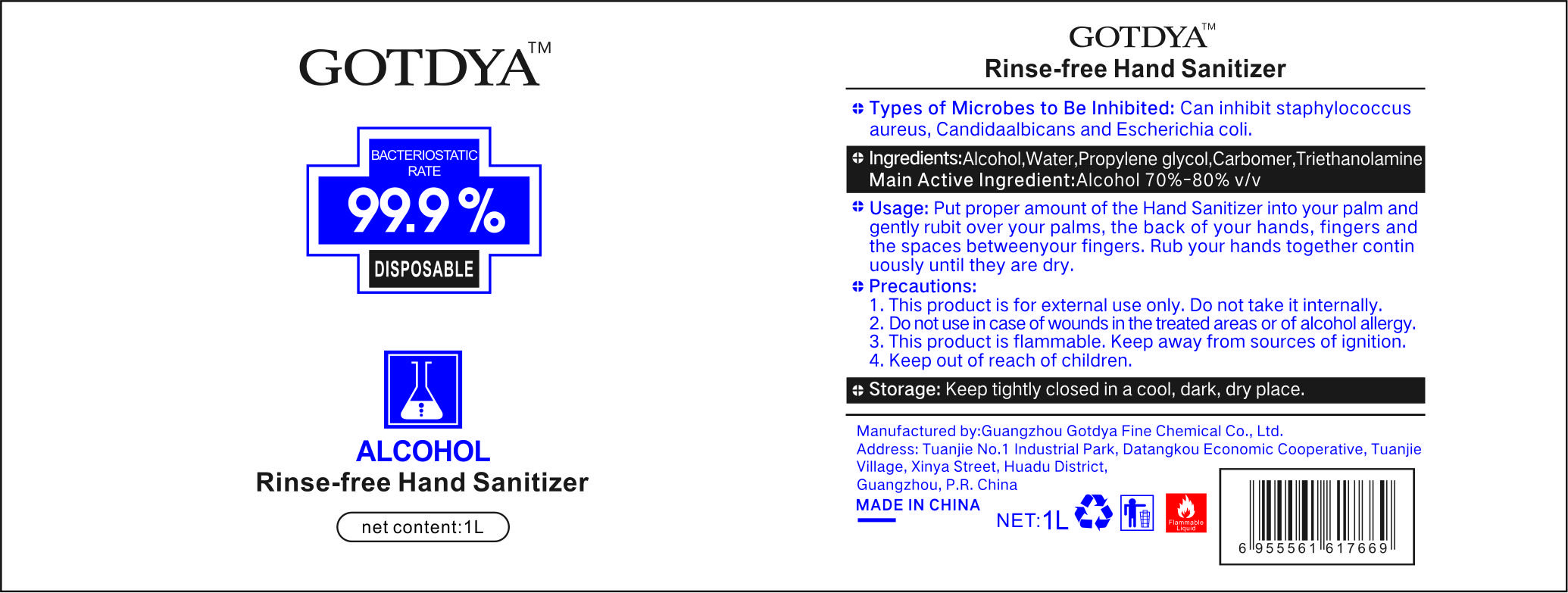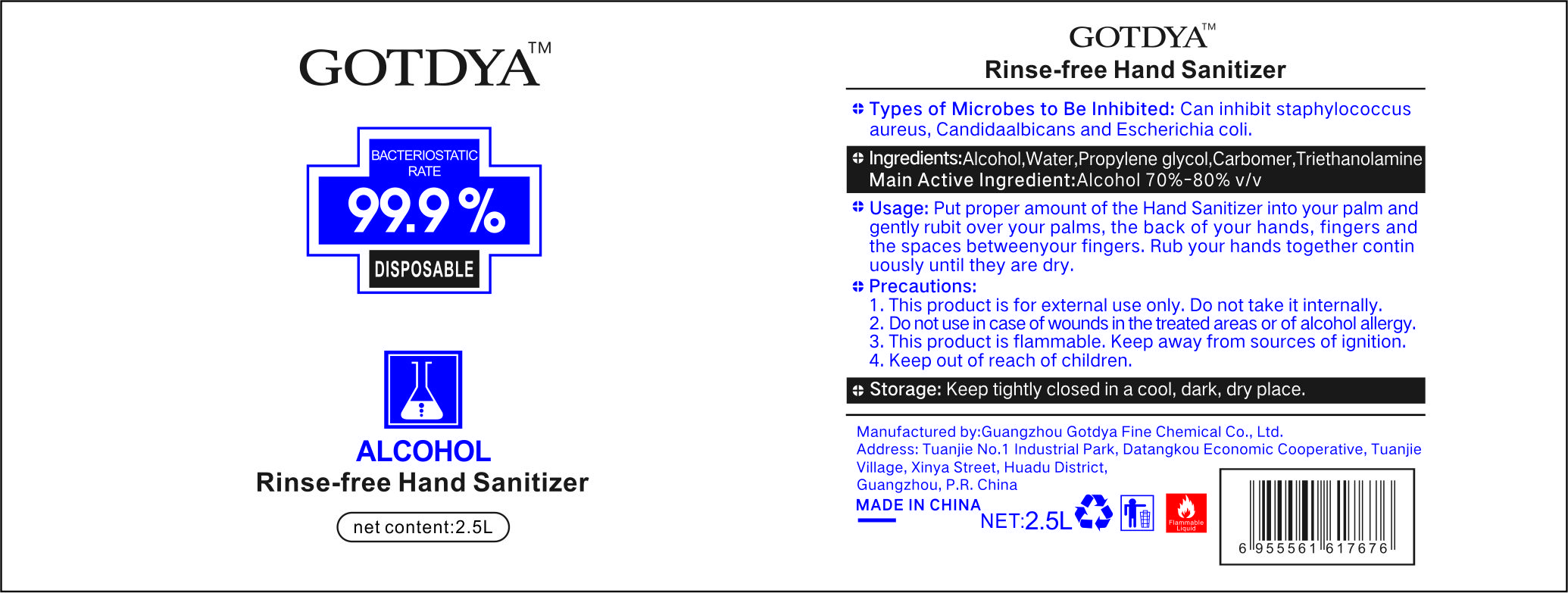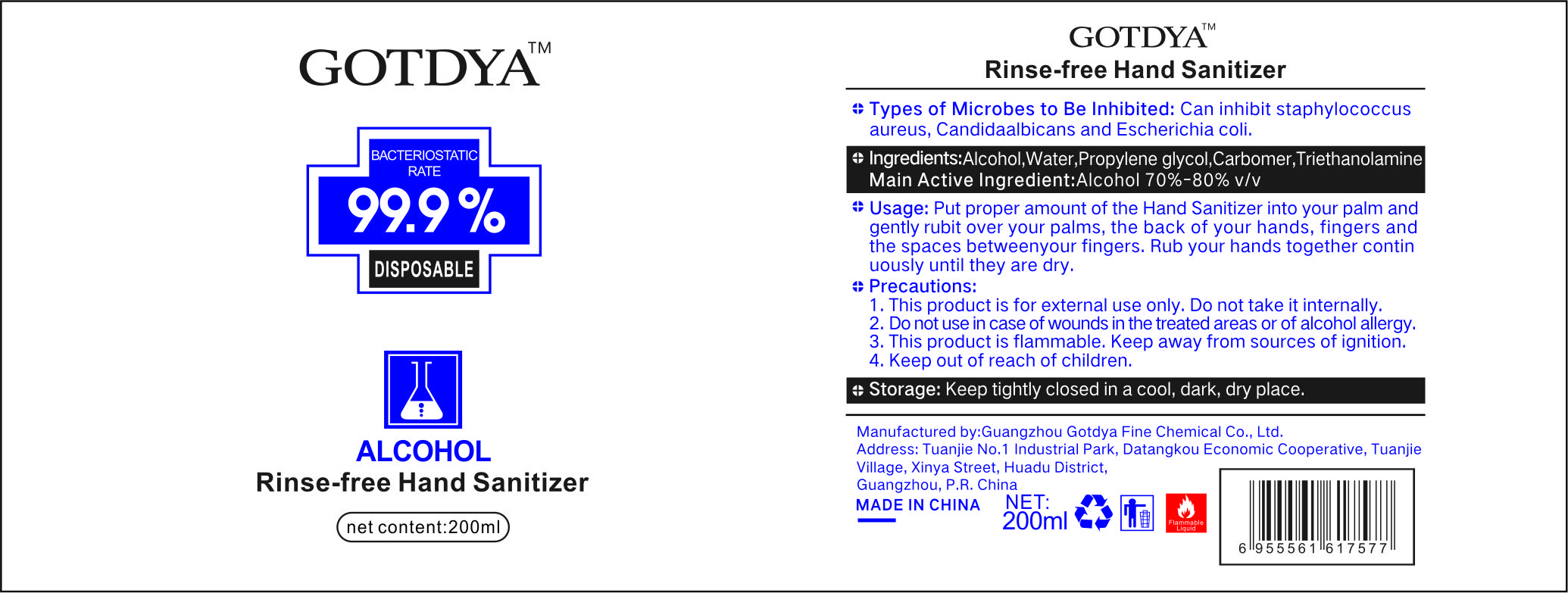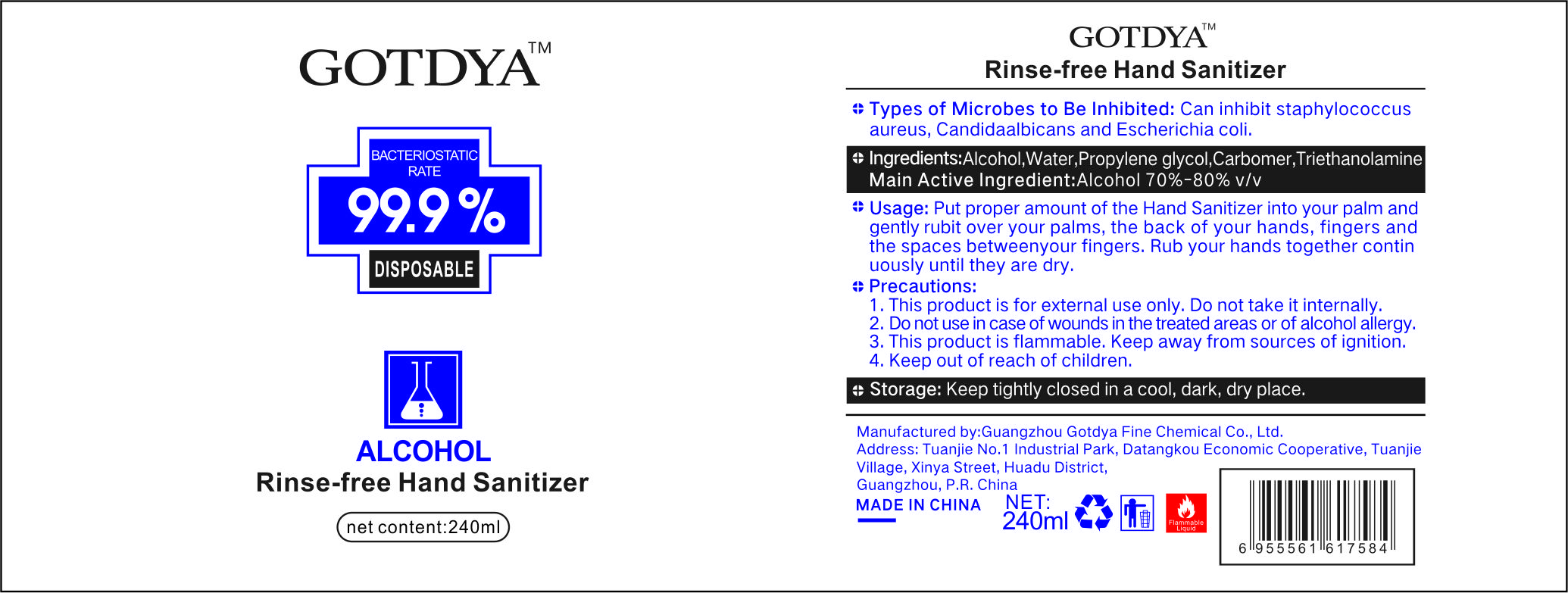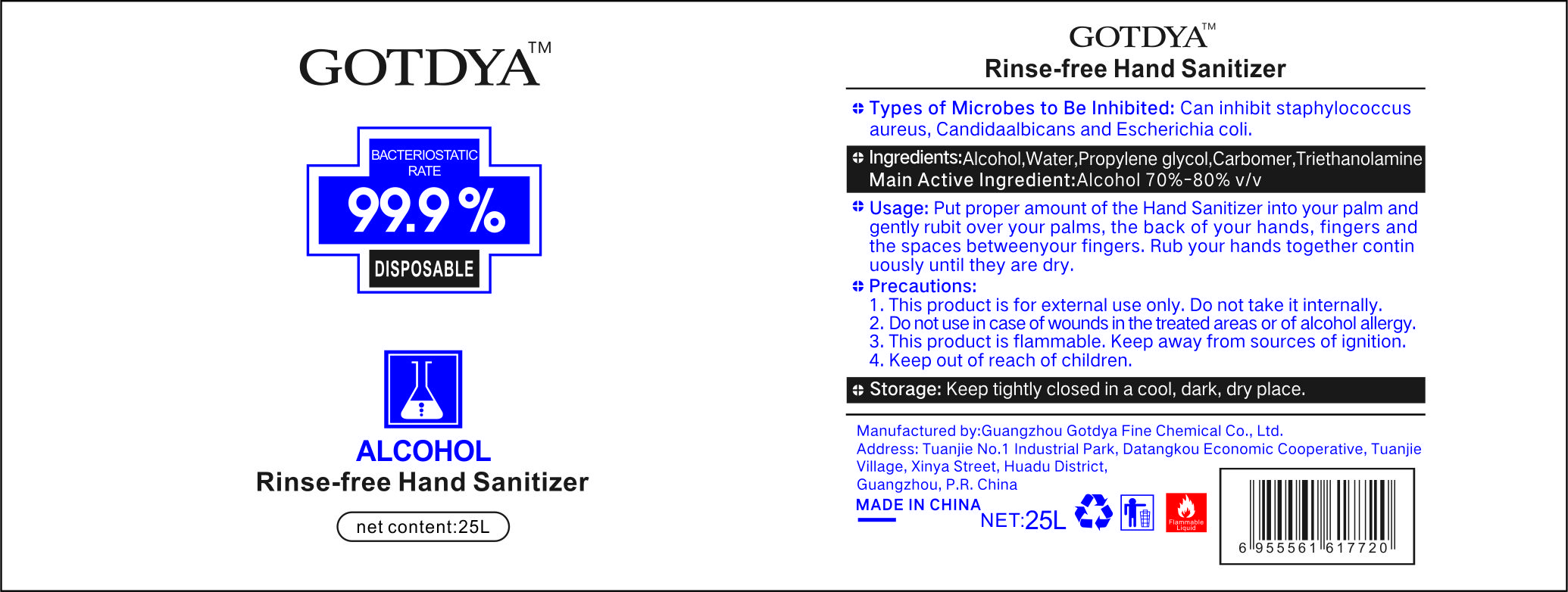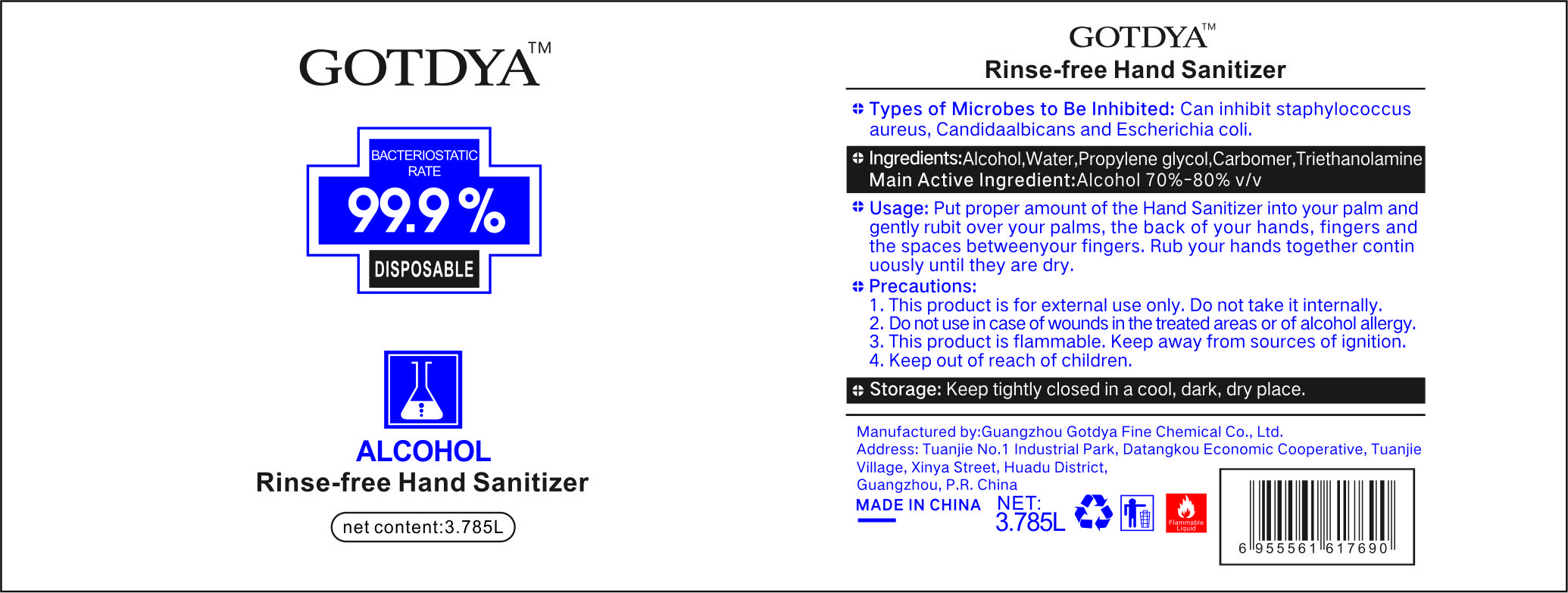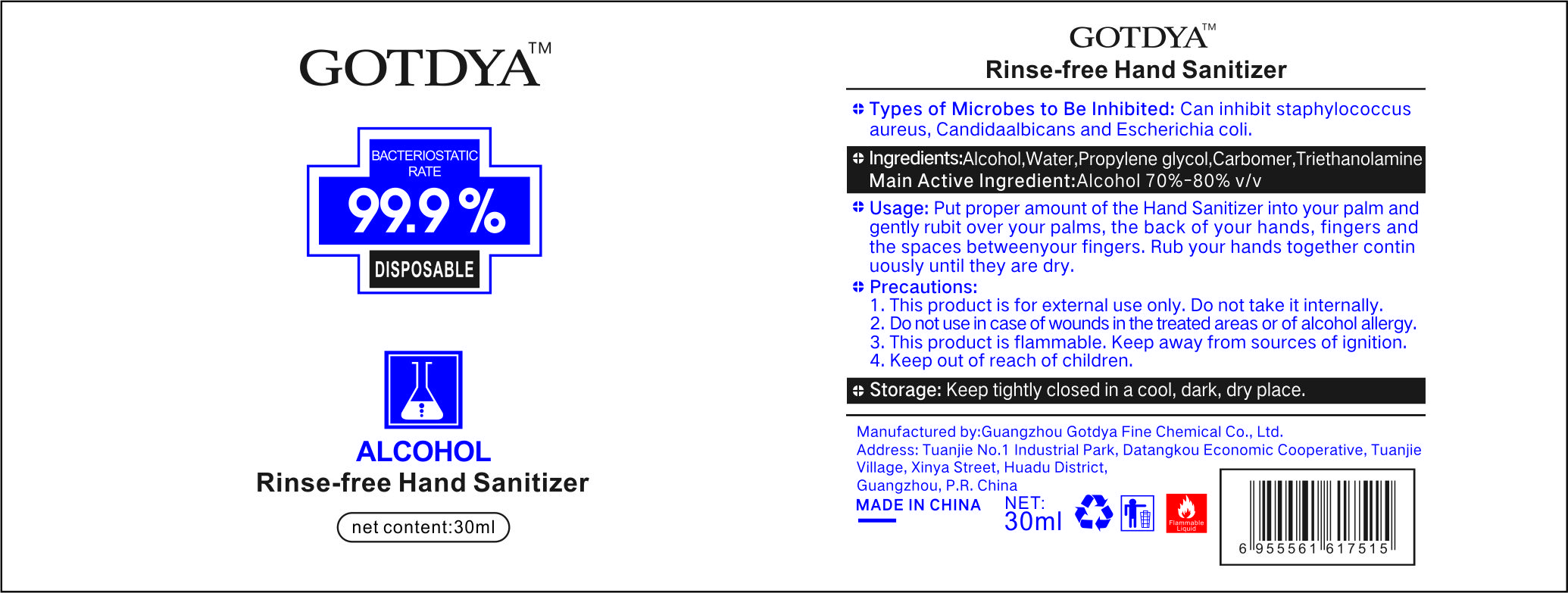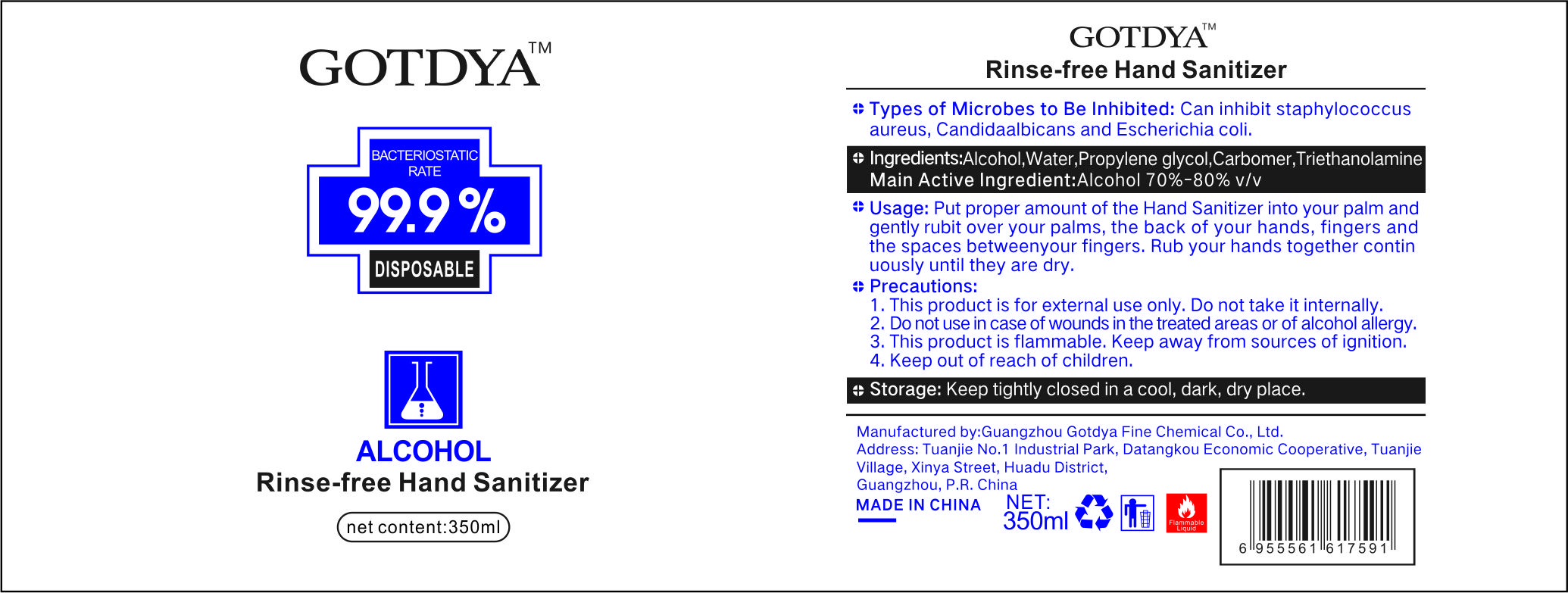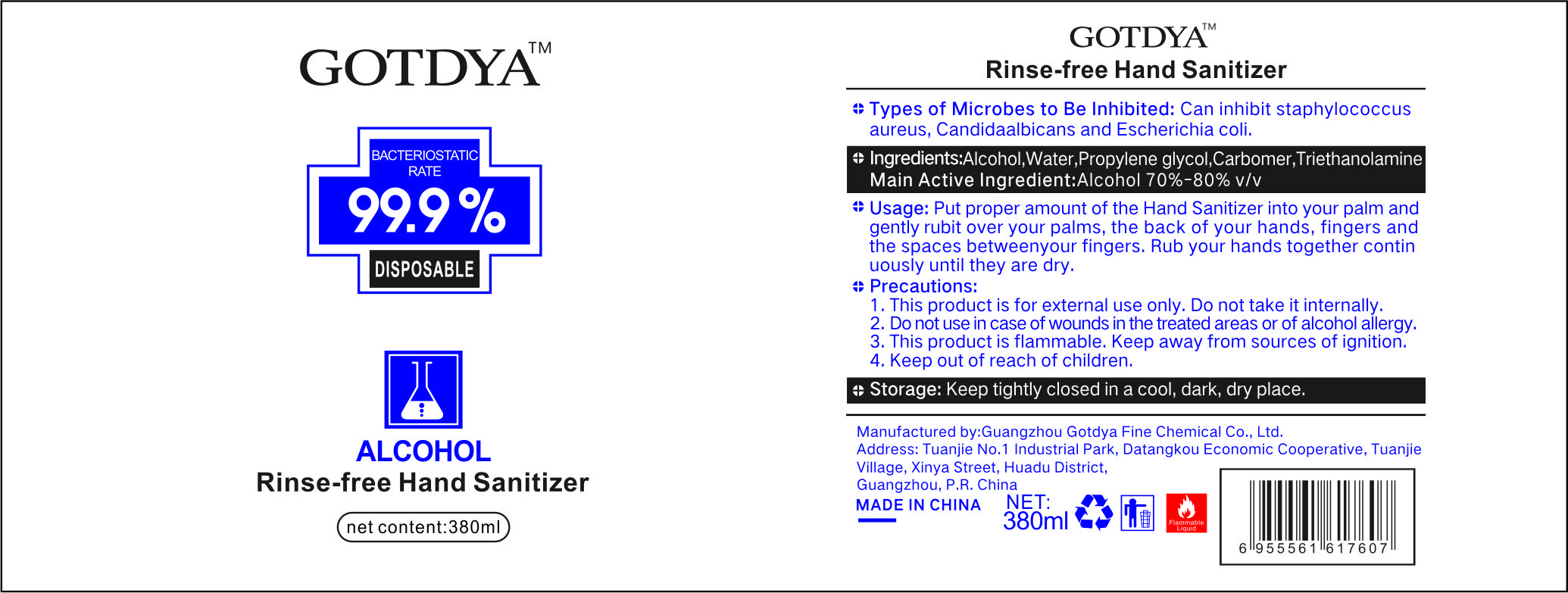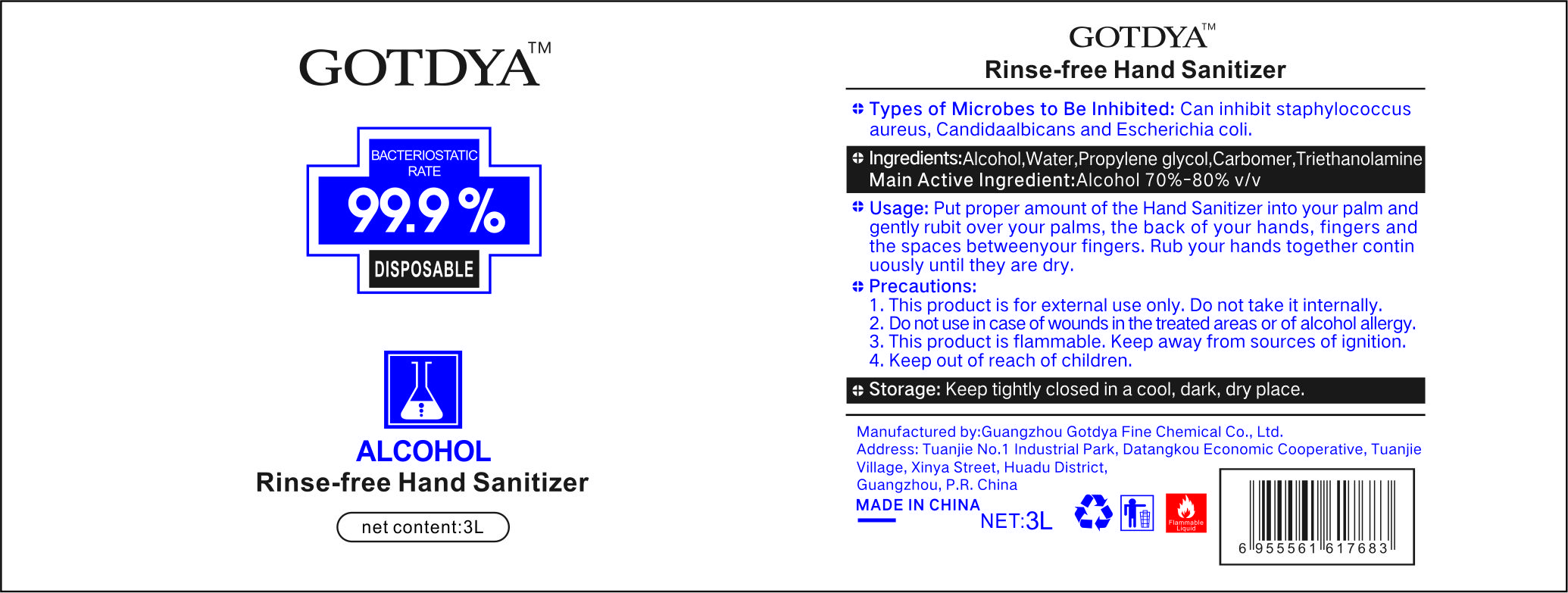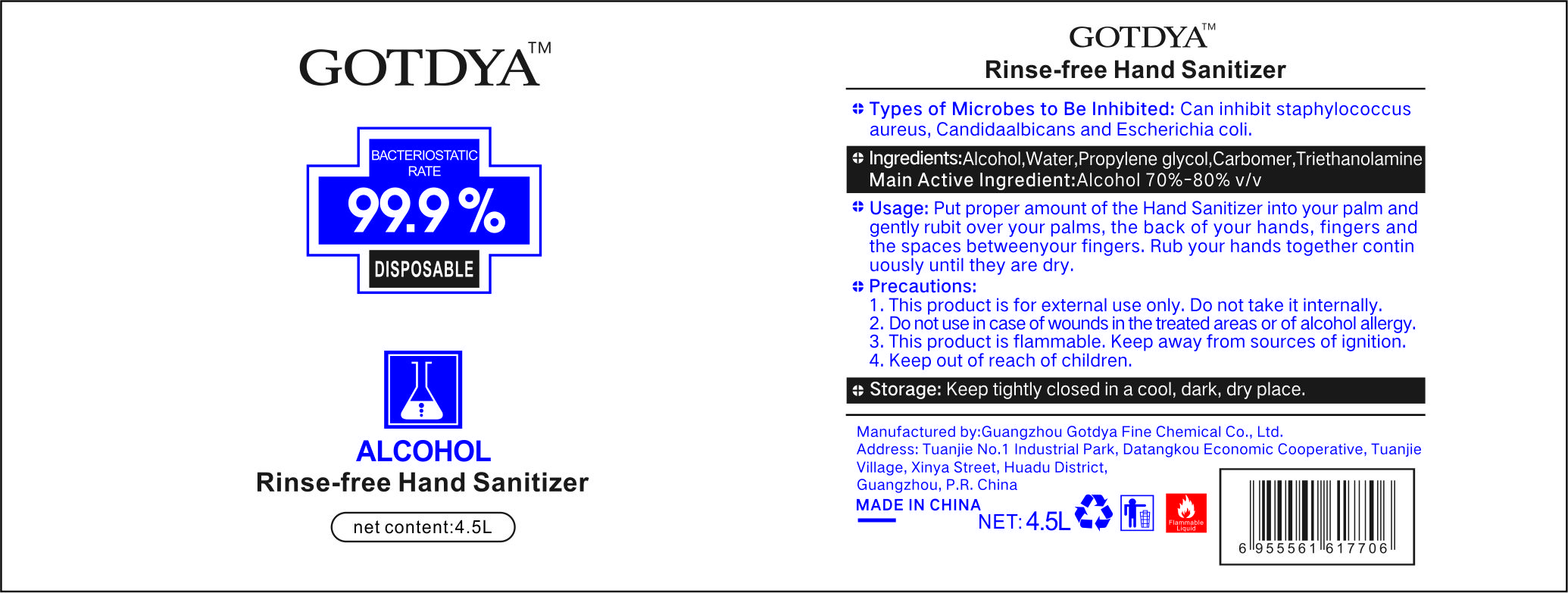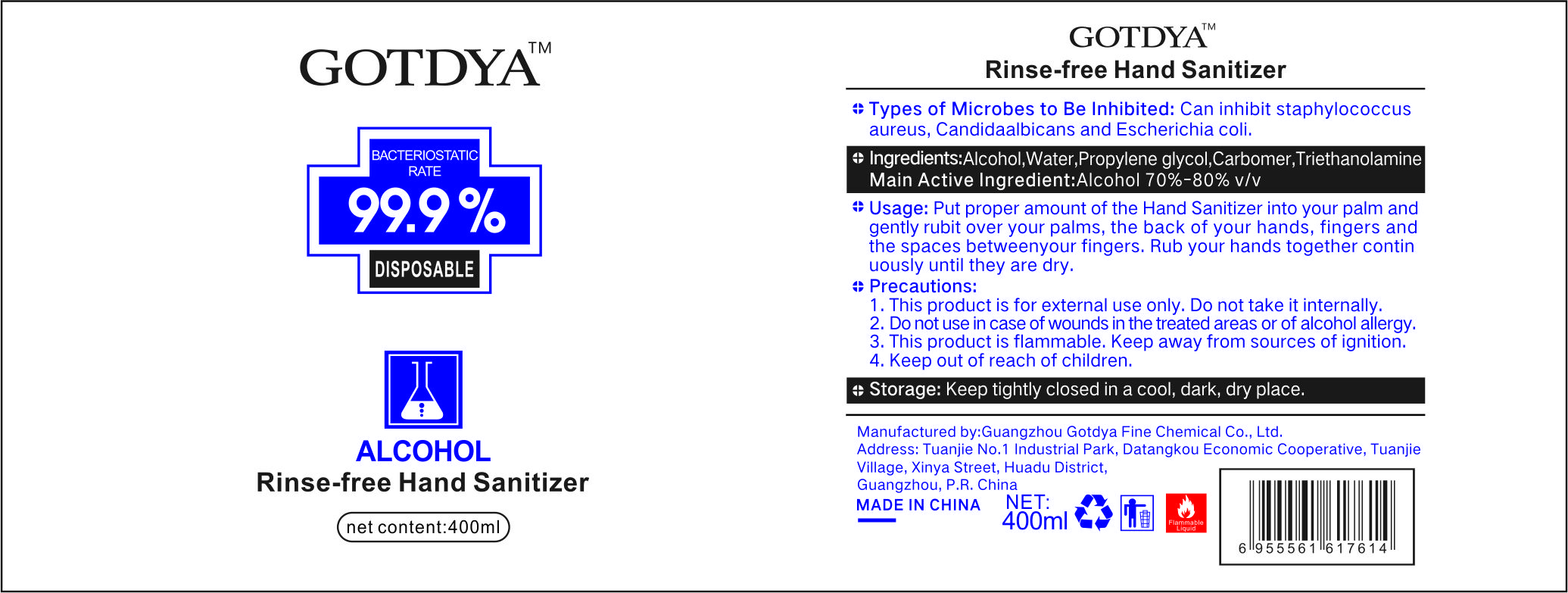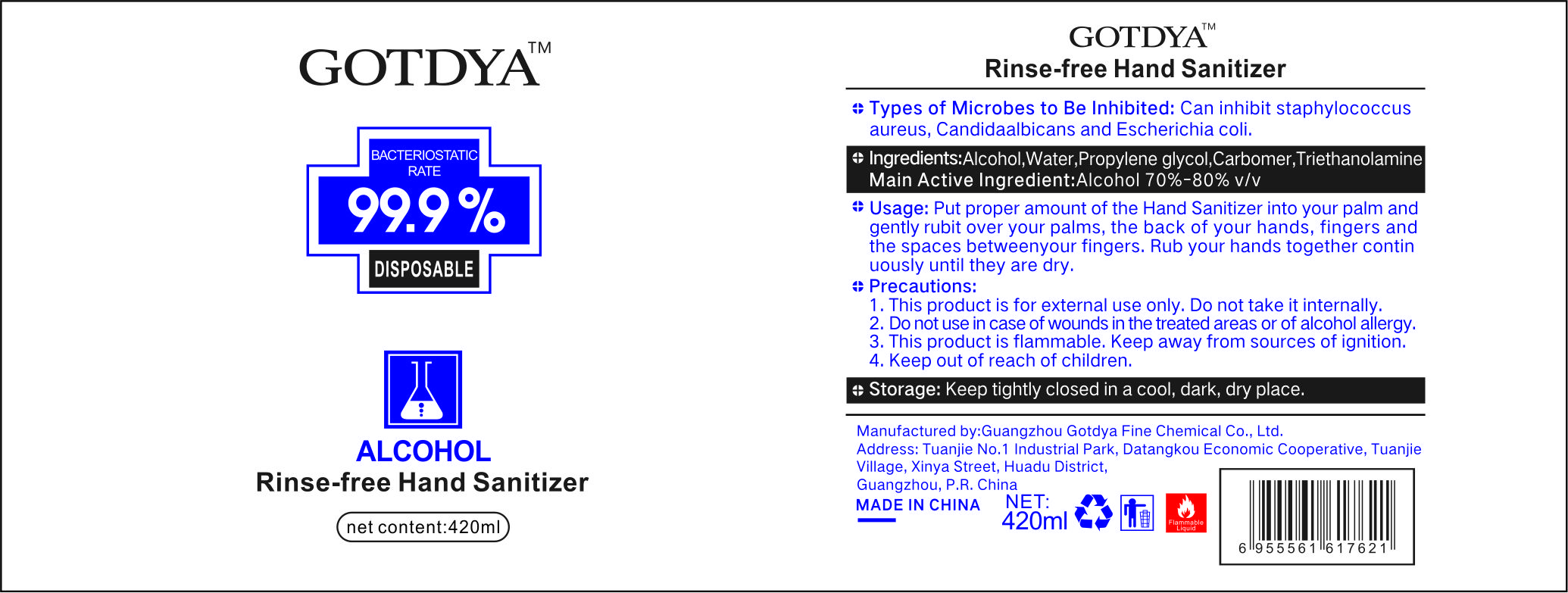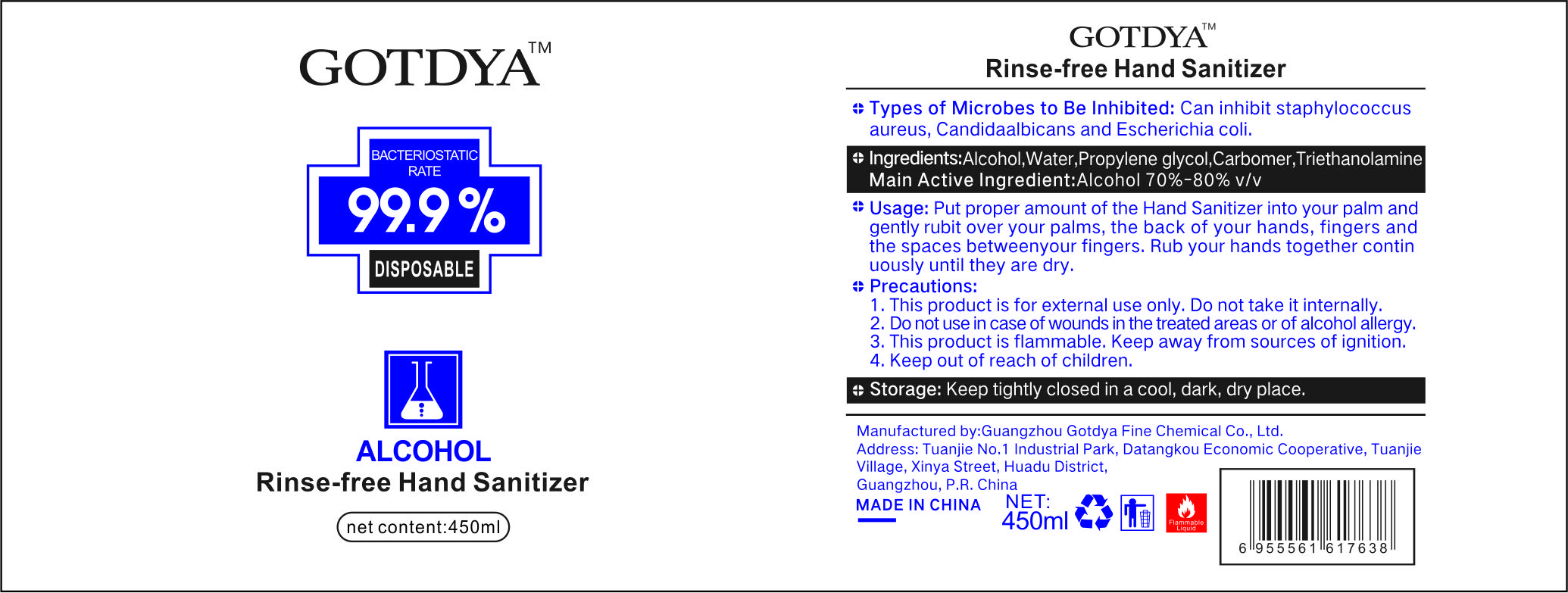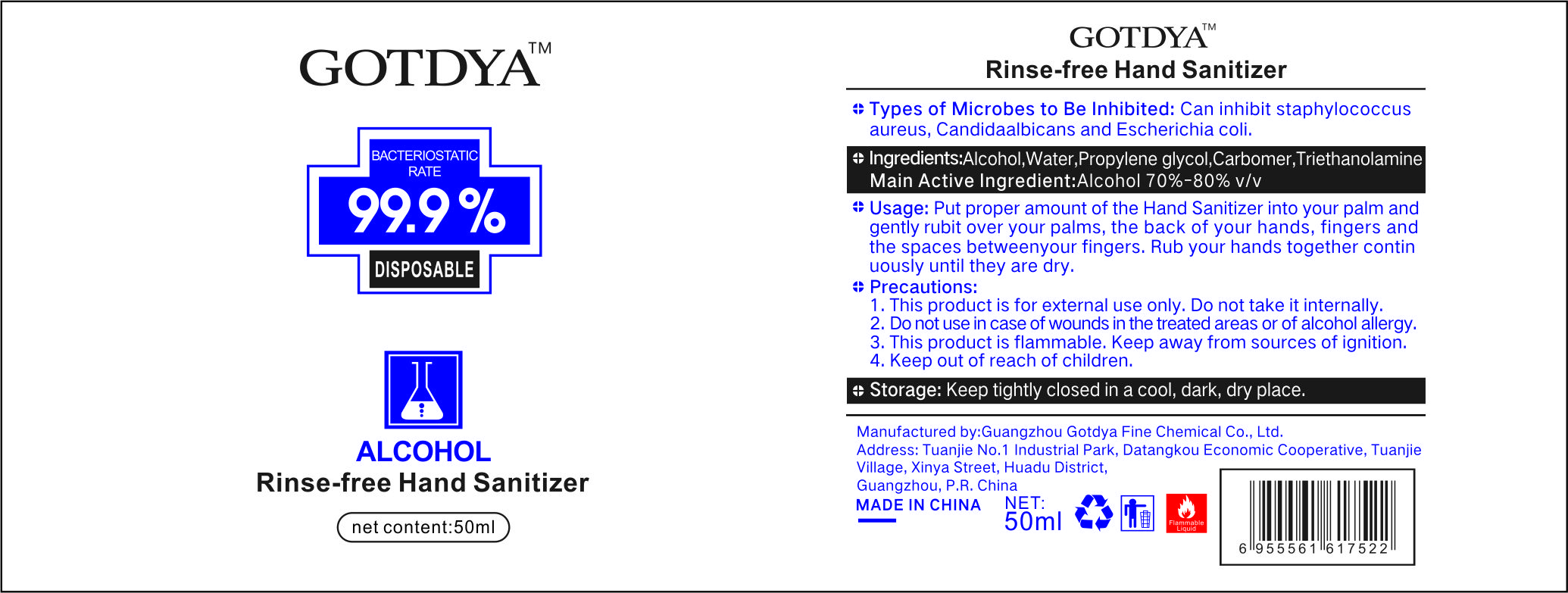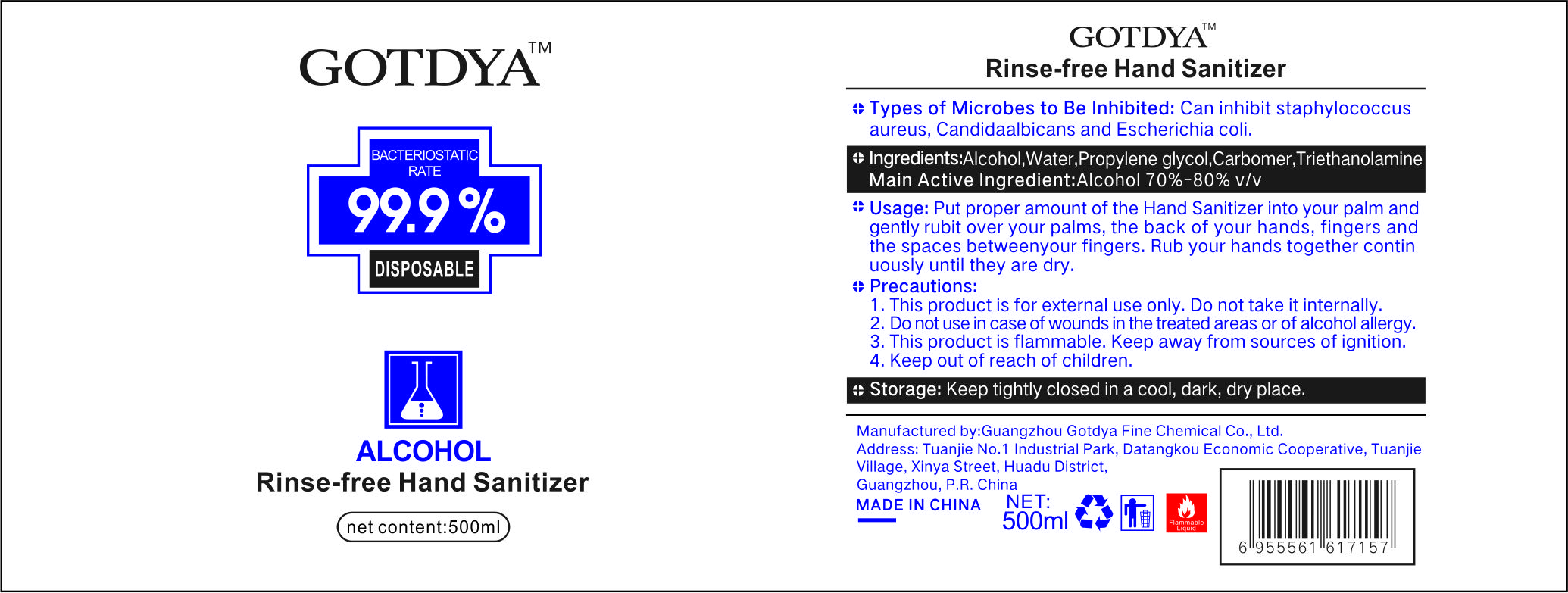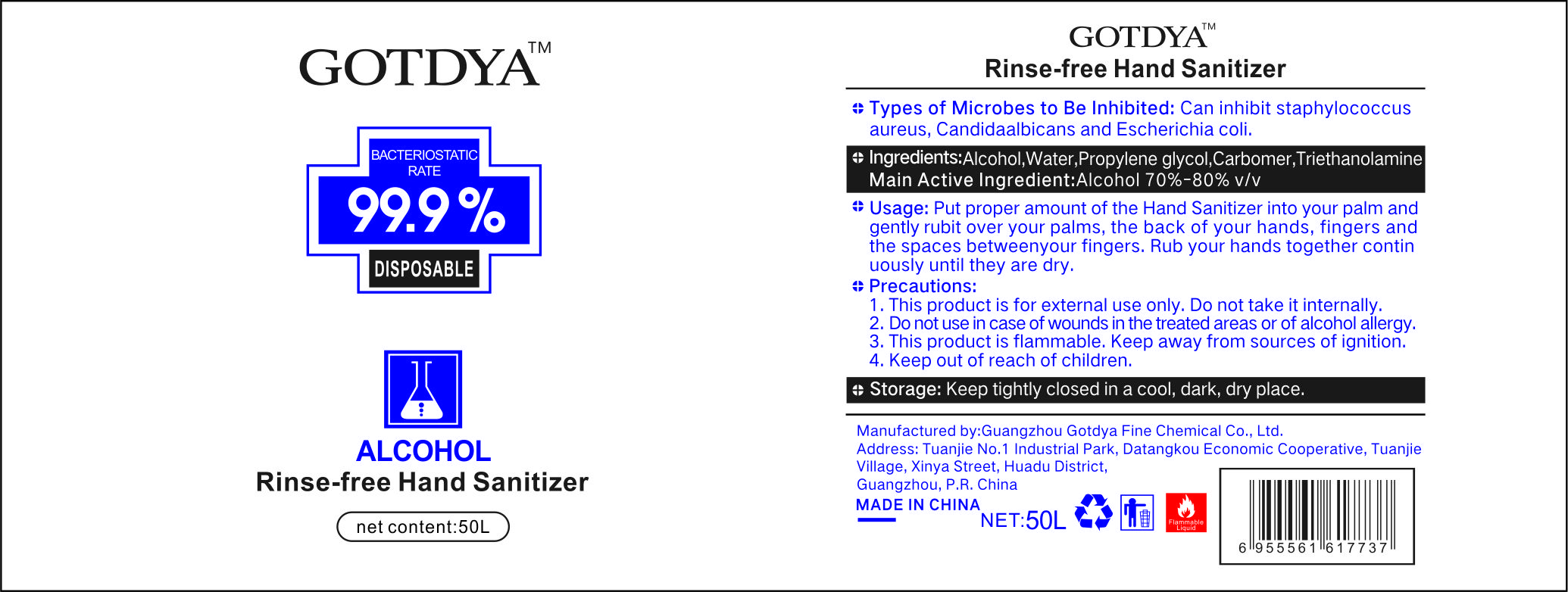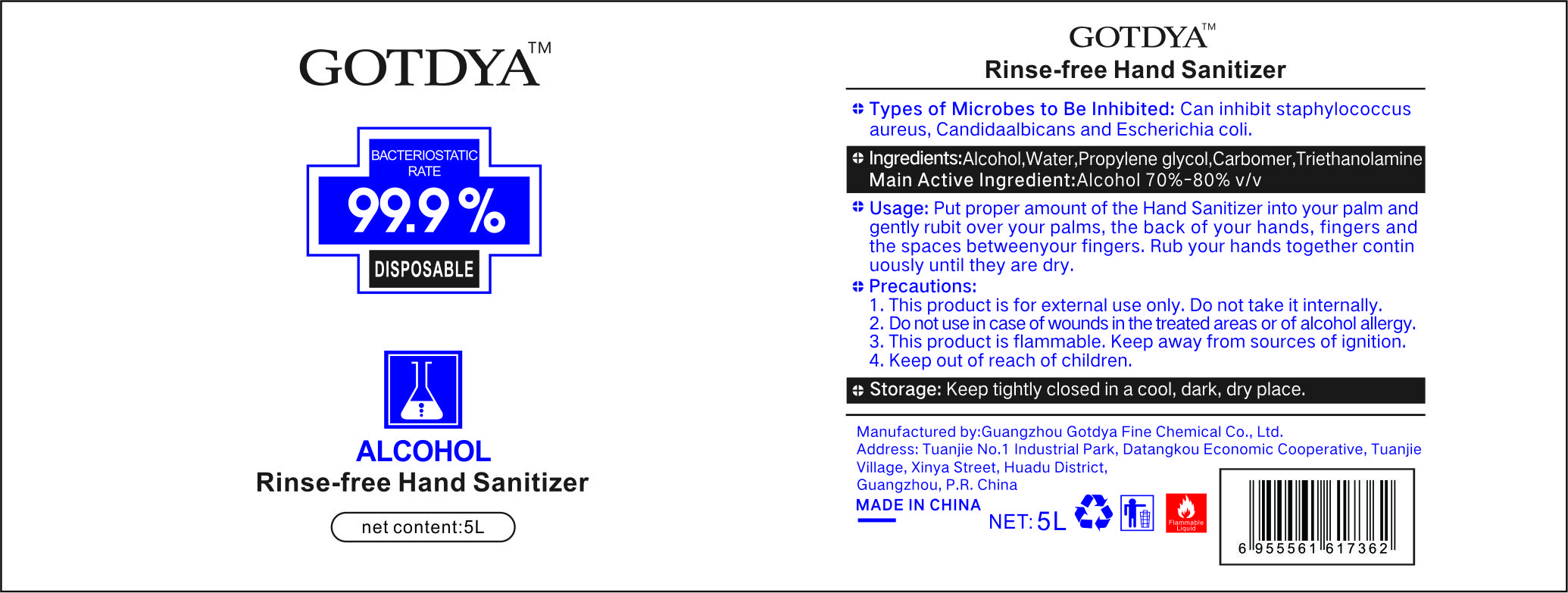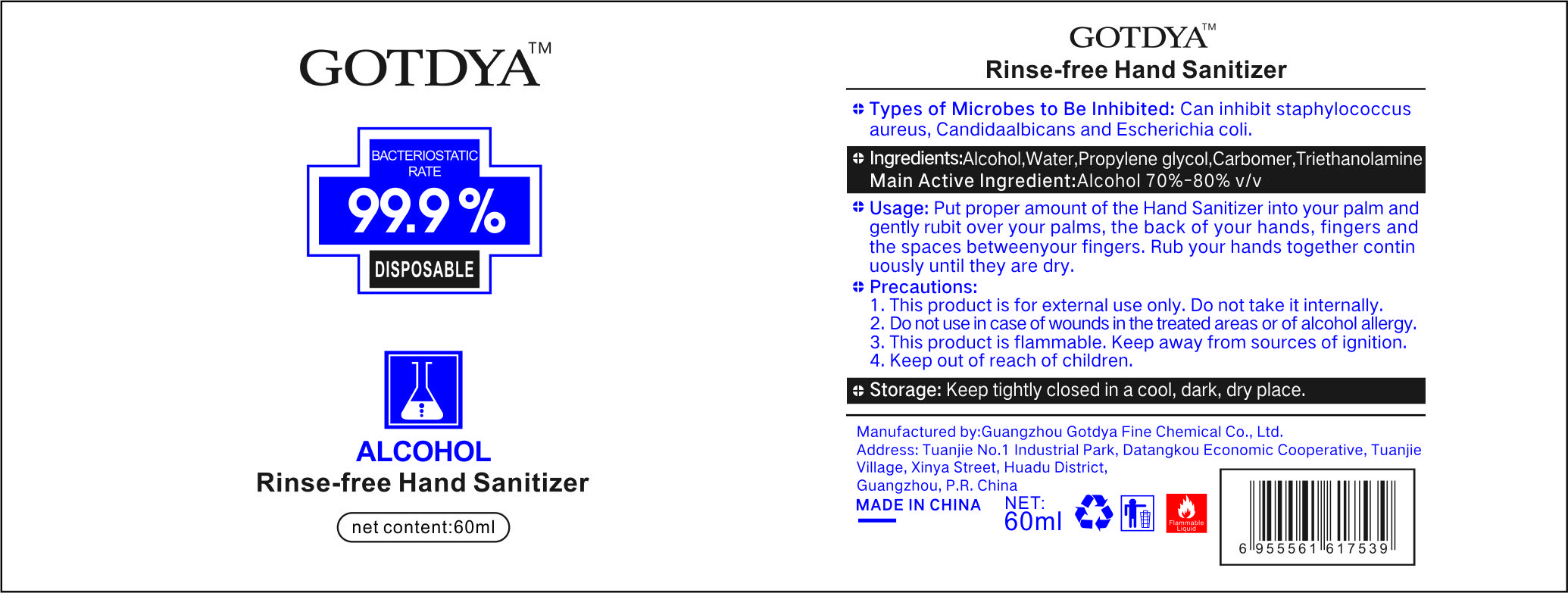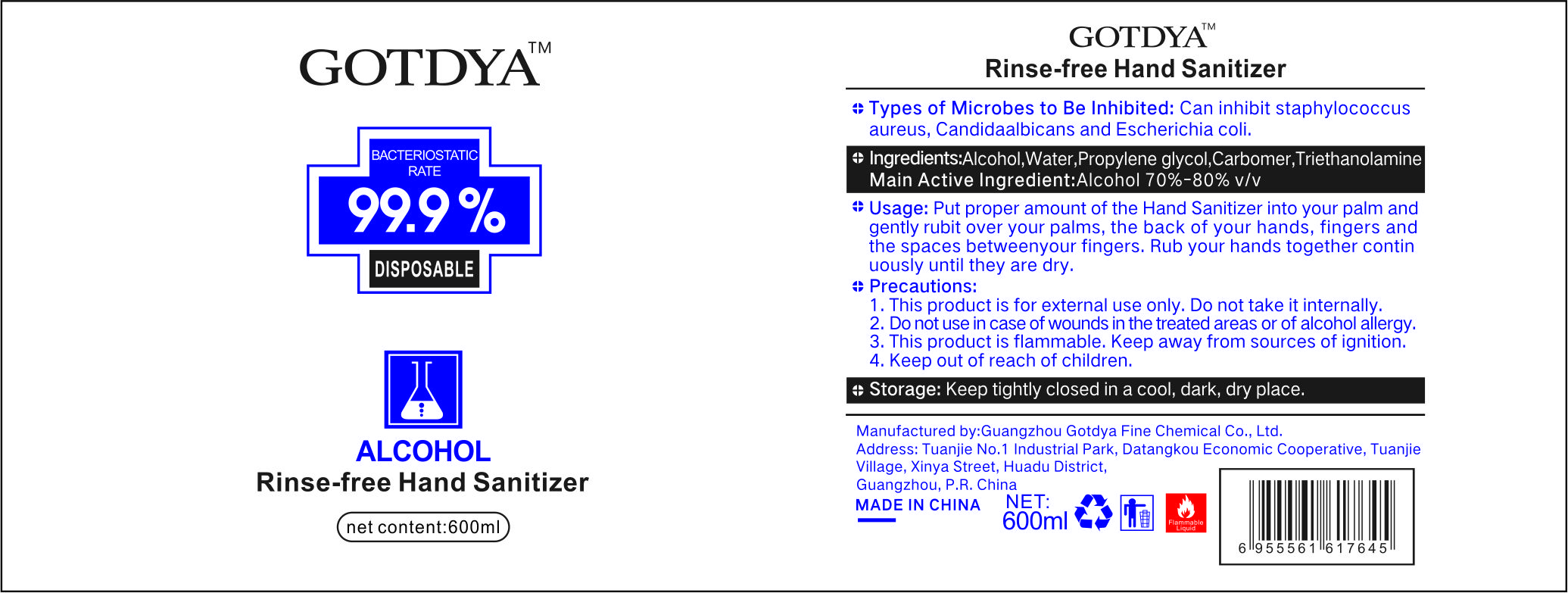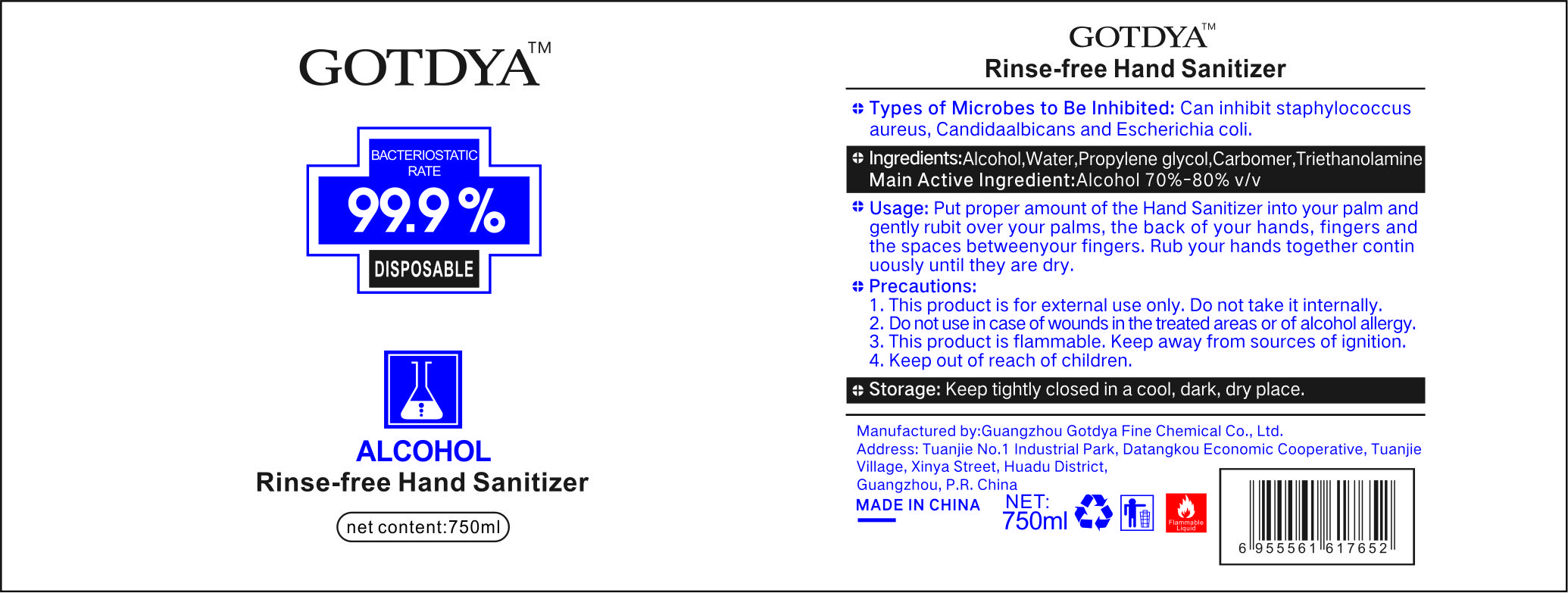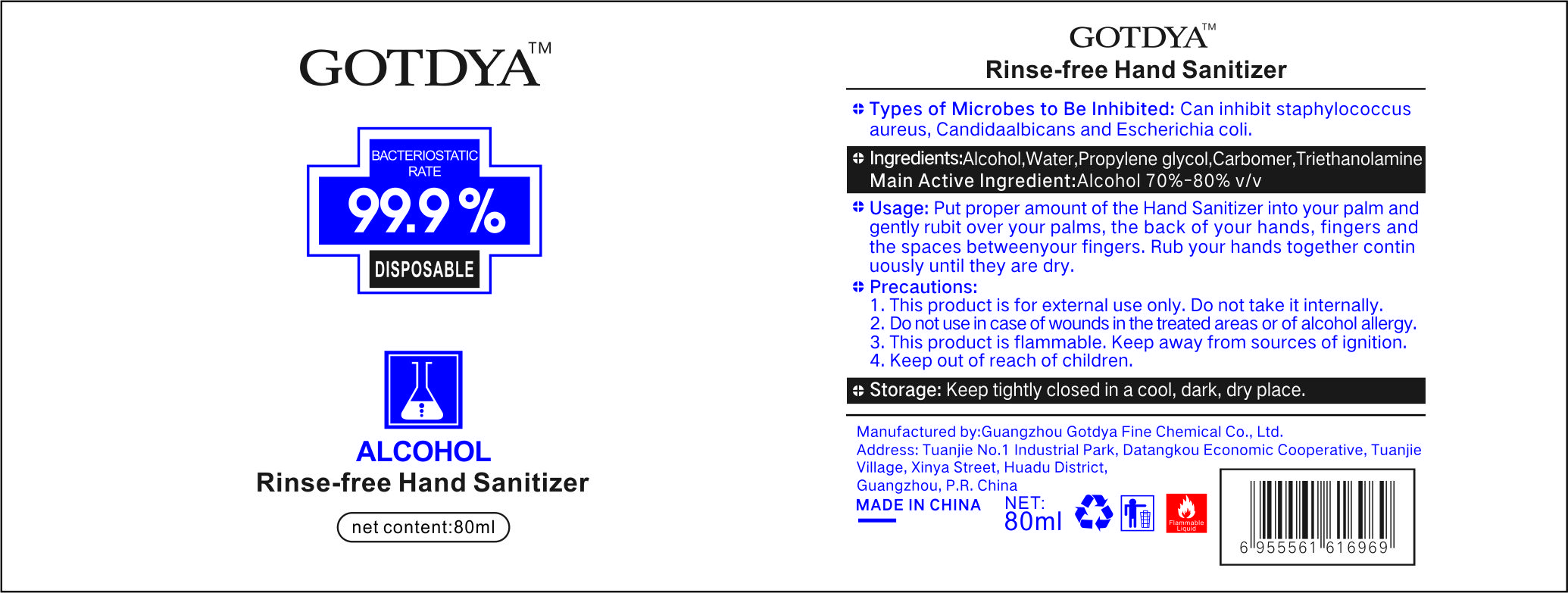 DRUG LABEL: Rinse-free Hand Sanitizer
NDC: 76591-101 | Form: GEL
Manufacturer: Guangzhou Gotdya Fine Chemical Co., Ltd.
Category: otc | Type: HUMAN OTC DRUG LABEL
Date: 20200803

ACTIVE INGREDIENTS: ALCOHOL 76 mL/100 mL
INACTIVE INGREDIENTS: WATER; TROLAMINE; CARBOMER HOMOPOLYMER, UNSPECIFIED TYPE; PROPYLENE GLYCOL

Rinse-free Hand Sanitizer

GOTDYA Rinse-free Hand Sanitizer

Active Ingredient(s)

Alcohol 70%-80% v/v

Purpose

Hand Sanitizer

Use

Types of Microbes to Be Inhibited: Can inhibit staphylococcus aureus, Candidaalbicans and Escherichia coli.

Warnings

This product is for external use only. Do not take it internally.

This product is flammable. Keep away from sources of ignition.

Do not use in case of wounds in the treated areas or of alcohol allergy.

This product is flammable. Keep away from sources of ignition.

Keep out of reach of children.

WHEN USING

Put proper amount of the Hand Sanitizer into your palm and gently rubit over your palms, the back of your hands, fingers and the spaces betweenyour fingers. Rub your hands together continuously until they are dry.

Keep out of reach of children.

Do not use in case of wounds in the treated areas or of alcohol allergy.

Keep out of reach of children.

Directions

Put proper amount of the Hand Sanitizer into your palm and gently rubit over your palms, the back of your hands, fingers and the spaces betweenyour fingers. Rub your hands together continuously until they are dry.

Keep out of reach of children.

Other information

- Storage: Keep tightly closed in a cool, dark, dry place.

Inactive ingredients

WATER
PROPYLENE GLYCOL
TRIETHANOLAMINE
CARBOMER